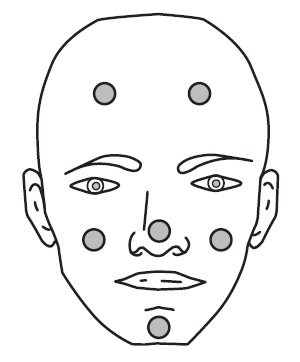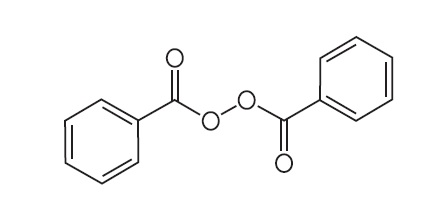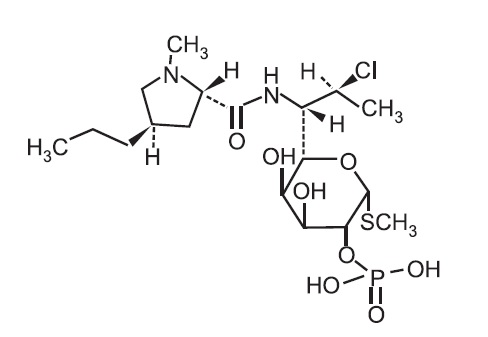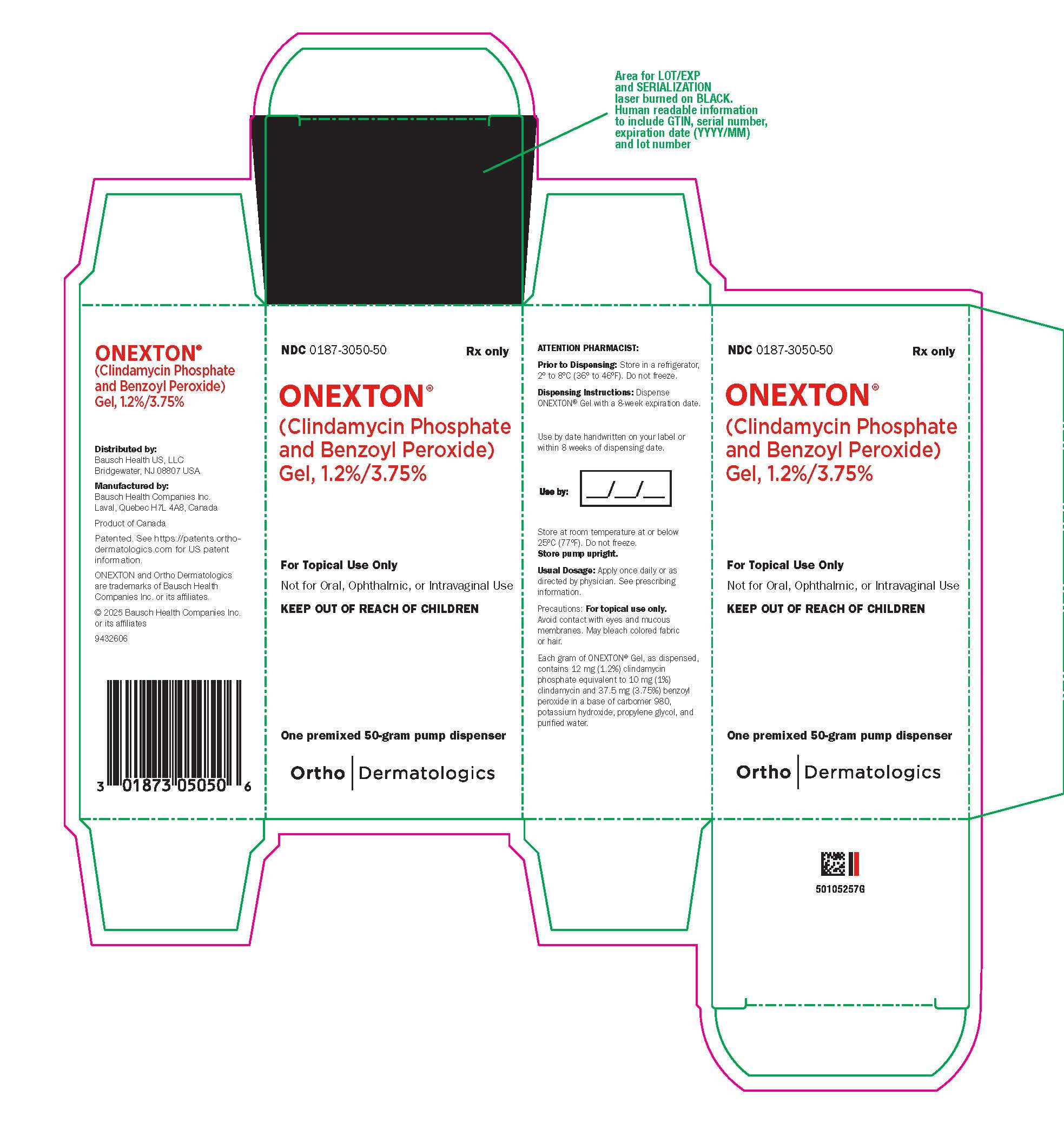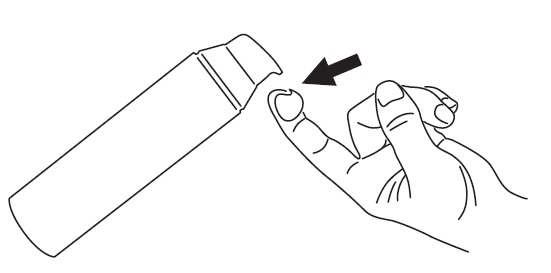 DRUG LABEL: ONEXTON
NDC: 0187-3050 | Form: GEL
Manufacturer: Bausch Health US, LLC
Category: prescription | Type: HUMAN PRESCRIPTION DRUG LABEL
Date: 20250723

ACTIVE INGREDIENTS: CLINDAMYCIN PHOSPHATE 10 mg/1 g; BENZOYL PEROXIDE 37.5 mg/1 g
INACTIVE INGREDIENTS: WATER; CARBOMER HOMOPOLYMER TYPE C (ALLYL PENTAERYTHRITOL CROSSLINKED); PROPYLENE GLYCOL; POTASSIUM HYDROXIDE

HIGHLIGHTS OF PRESCRIBING INFORMATION

These highlights do not include all the information needed to use ONEXTON Gel safely and effectively. See full prescribing information for ONEXTON Gel.
ONEXTON® (clindamycin phosphate and benzoyl peroxide) gel, 1.2%/3.75% for topical use
Initial U.S. Approval: 2000

1 INDICATIONS AND USAGE

ONEXTON Gel is a combination of clindamycin phosphate (a lincosamide antibacterial) and benzoyl peroxide indicated for the topical treatment of acne vulgaris in patients 12 years of age and older. (1)

2 DOSAGE AND ADMINISTRATION

  - Apply a pea-sized amount of ONEXTON Gel to the face once daily. (2)
  - Not for oral, ophthalmic, or intravaginal use. (2)

3 DOSAGE FORMS AND STRENGTHS

Gel, 1.2% clindamycin phosphate/3.75% benzoyl peroxide

4 CONTRAINDICATIONS

ONEXTON Gel is contraindicated in:

- Patients who have demonstrated hypersensitivity (e.g., anaphylaxis) to clindamycin, benzoyl peroxide, any components of the formulation, or lincomycin. (4.1)
- Patients with a history of regional enteritis, ulcerative colitis, or antibiotic-associated colitis. (4.2)

5 WARNINGS AND PRECAUTIONS

- Colitis: Clindamycin can cause severe colitis, which may result in death. Diarrhea, bloody diarrhea, and colitis (including pseudomembranous colitis) have been reported with the use of clindamycin. ONEXTON Gel should be discontinued if significant diarrhea occurs. (5.1)
- Ultraviolet Light and Environmental Exposure: Minimize sun exposure following drug application. (5.2)

6 ADVERSE REACTIONS

The most common adverse reactions are: burning sensation (0.4%); contact dermatitis (0.4%); pruritus (0.4%); and rash (0.4%). (6.1)

To report SUSPECTED ADVERSE REACTIONS, contact Bausch Health US, LLC at 1-800-321-4576 or FDA at 1-800-FDA-1088 or www.fda.gov/medwatch.

7 DRUG INTERACTIONS

Avoid using ONEXTON Gel in combination with topical or oral erythromycin-containing products because of its clindamycin component. (7.1)

FULL PRESCRIBING INFORMATION

1 INDICATIONS AND USAGE

ONEXTON® (clindamycin phosphate and benzoyl peroxide) Gel, 1.2%/3.75% is indicated for the topical treatment of acne vulgaris in patients 12 years of age and older.

2 DOSAGE AND ADMINISTRATION

Before applying ONEXTON Gel, wash the face gently with a mild soap, rinse with warm water, and pat the skin dry. Apply a pea-sized amount of ONEXTON Gel to the face once daily. Avoid the eyes, mouth, mucous membranes, or areas of broken skin.

Use of ONEXTON Gel beyond 12 weeks has not been evaluated.

ONEXTON Gel is not for oral, ophthalmic, or intravaginal use.

3 DOSAGE FORMS AND STRENGTHS

Gel, 1.2%/3.75%

Each gram of ONEXTON Gel contains 12 mg (1.2%) clindamycin phosphate, equivalent to 10 mg (1%) clindamycin, and 37.5 mg (3.75%) benzoyl peroxide in a white to off-white, opaque, smooth gel.

4 CONTRAINDICATIONS

4.1 Hypersensitivity

ONEXTON Gel is contraindicated in those individuals who have shown hypersensitivity to clindamycin, benzoyl peroxide, any components of the formulation, or lincomycin. Anaphylaxis, as well as allergic reactions leading to hospitalization, has been reported in postmarketing use with ONEXTON Gel [see Postmarketing Experience (6.2)].

4.2 Colitis/Enteritis

ONEXTON Gel is contraindicated in patients with a history of regional enteritis, ulcerative colitis, or antibiotic-associated colitis [see Warnings and Precautions (5.1)].

5 WARNINGS AND PRECAUTIONS

5.1 Colitis

Systemic absorption of clindamycin has been demonstrated following topical use of clindamycin. Diarrhea, bloody diarrhea, and colitis (including pseudomembranous colitis) have been reported with the use of topical and systemic clindamycin. If significant diarrhea occurs, ONEXTON Gel should be discontinued.

Severe colitis has occurred following oral and parenteral administration of clindamycin with an onset of up to several weeks following cessation of therapy. Antiperistaltic agents such as opiates and diphenoxylate with atropine may prolong and/or worsen severe colitis. Severe colitis may result in death.

Studies indicate toxin(s) produced by Clostridia is one primary cause of antibiotic-associated colitis. The colitis is usually characterized by severe persistent diarrhea and severe abdominal cramps and may be associated with the passage of blood and mucus. Stool cultures for Clostridium difficile and stool assay for C. difficile toxin may be helpful diagnostically.

5.2 Ultraviolet Light and Environmental Exposure

Minimize sun exposure (including use of tanning beds or sun lamps) following drug application.

5.3 Concomitant Topical Medications

Concomitant topical acne therapy should be used with caution since a possible cumulative irritancy effect may occur, especially with the use of peeling, desquamating, or abrasive agents. If irritancy or dermatitis occurs, reduce frequency of application or temporarily interrupt treatment and resume once the irritation subsides. Treatment should be discontinued if the irritation persists.

6 ADVERSE REACTIONS

The following adverse reaction is described in more detail in the Warnings and Precautions section of the label:

- Colitis [see Warnings and Precautions (5.1)].

6.1 Clinical Trials Experience

Because clinical trials are conducted under widely varying conditions, adverse reaction rates observed in clinical trials of a drug cannot be directly compared to rates observed in clinical trials of another drug and may not reflect the rates observed in clinical practice.

These adverse reactions occurred in less than 0.5% of subjects treated with ONEXTON Gel: burning sensation (0.4%); contact dermatitis (0.4%); pruritus (0.4%); and rash (0.4%).

During the clinical trial, subjects were assessed for local cutaneous signs and symptoms of erythema, scaling, itching, burning and stinging. Most local skin reactions either were the same as baseline or increased and peaked around Week 4 and were near or improved from baseline levels by Week 12. The percentage of subjects that had symptoms present before treatment (at baseline), during treatment, and the percent with symptoms present at Week 12 are shown in Table 1.

Table 1: Percent of Subjects with Local Skin Reactions. Results from the Phase 3 Trial (N = 243)
 | Before Treatment (Baseline) |  |  | During Treatment |  |  | End of Treatment (Week 12)
 | Mild | Mod.* | Severe | Mild | Mod.* | Severe | Mild | Mod.* | Severe
Erythema | 20 | 6 | 0 | 28 | 5 | <1 | 15 | 2 | 0
Scaling | 10 | 1 | 0 | 19 | 3 | 0 | 10 | <1 | 0
Itching | 14 | 3 | <1 | 15 | 3 | 0 | 7 | 2 | 0
Burning | 5 | <1 | <1 | 7 | 1 | <1 | 3 | <1 | 0
Stinging | 5 | <1 | 0 | 7 | 0 | <1 | 3 | 0 | <1

*Mod. = Moderate

6.2 Postmarketing Experience

Because postmarketing adverse reactions are reported voluntarily from a population of uncertain size, it is not always possible to reliably estimate their frequency or establish a causal relationship to drug exposure.

Anaphylaxis, as well as allergic reactions leading to hospitalizations, has been reported in postmarketing use of products containing clindamycin phosphate/benzoyl peroxide.

7 DRUG INTERACTIONS

7.1 Erythromycin

Avoid using ONEXTON Gel in combination with topical or oral erythromycin-containing products due to its clindamycin component. In vitro studies have shown antagonism between erythromycin and clindamycin. The clinical significance of this in vitro antagonism is not known.

7.2 Neuromuscular Blocking Agents

Clindamycin has been shown to have neuromuscular blocking properties that may enhance the action of other neuromuscular blocking agents. ONEXTON Gel should be used with caution in patients receiving such agents.

8 USE IN SPECIFIC POPULATIONS

8.1 Pregnancy

TERATOGENIC EFFECTS

Risk Summary

There are no available data on ONEXTON Gel use in pregnant women to evaluate a drug-associated risk of major birth defects, miscarriage, or adverse maternal or fetal outcomes. The limited published data on use of clindamycin in pregnant women with exposure during the first trimester are insufficient to inform a drug-associated risk of pregnancy-related adverse outcomes (see Data). In limited published clinical trials with pregnant women, the systemic administration of clindamycin during the second and third trimesters has not been associated with an increased frequency of major birth defects.

In animal reproduction studies, clindamycin did not cause malformations or embryo-fetal development toxicity in pregnant rats and mice when administered during the period of organogenesis at systemic doses up to 240 times the maximum recommended human dose (MRHD) of 2.5 g ONEXTON Gel, based on body surface area (BSA) comparisons (see Data).

The estimated background risk of major birth defects and miscarriage for the indicated population is unknown. All pregnancies have a background risk of major birth defects, loss, and other adverse outcomes. In the U.S. general population, the estimated background risk of major birth defects and miscarriage in clinically recognized pregnancies is 2 to 4% and 15 to 20%, respectively.

Data

Human Data

In limited published trials in pregnant women administered clindamycin during the first trimester of pregnancy, there was no difference in the rate of major birth defects reported among in utero exposed infants compared to unexposed infants. These data cannot definitely establish or exclude any clindamycin-associated risk during pregnancy.

Animal Data

Animal reproductive/developmental toxicity studies have not been conducted with ONEXTON Gel or benzoyl peroxide. Developmental toxicity studies of clindamycin performed in pregnant rats and mice administered during the period of organogenesis at oral doses of up to 600 mg/kg/day (240 and 120 times the MRHD for clindamycin, respectively, based on BSA comparisons) or subcutaneous doses of up to 200 mg/kg/day (80 and 40 times the MRHD for clindamycin, respectively, based on BSA comparisons) revealed no malformations or embryo-fetal development toxicity.

8.2 Lactation

Risk Summary

There are no data on the presence of clindamycin or benzoyl peroxide in human milk, the effects on the breastfed child, or the effects on milk production following topical administration. However, clindamycin has been reported to be present in breast milk in small amounts following oral and parenteral administration. The developmental and health benefits of breastfeeding should be considered along with the mother’s clinical need for ONEXTON Gel and any potential adverse effects on the breastfed child from ONEXTON Gel or from the underlying maternal condition.

Clinical Considerations

If used during lactation and ONEXTON Gel is applied to the chest, care should be taken to avoid accidental ingestion by the infant.

8.4 Pediatric Use

Safety and effectiveness of ONEXTON Gel in pediatric patients under the age of 12 years have not been evaluated.

8.5 Geriatric Use

Clinical trials of ONEXTON Gel did not include sufficient numbers of subjects age 65 years and older to determine whether they respond differently from younger subjects.

11 DESCRIPTION

ONEXTON Gel is a combination product with two active ingredients in a white to off-white, opaque, smooth, aqueous gel formulation intended for topical use. Clindamycin phosphate is a water-soluble ester of the semisynthetic antibiotic produced by a 7(S)-chloro-substitution of the 7(R)‑hydroxyl group of the parent antibiotic lincomycin.

The chemical name for clindamycin phosphate is Methyl 7-chloro-6,7,8-trideoxy-6- (1-methyl-trans-4-propyl-L-2-pyrrolidinecarboxamido)-1-thio-L-threo-α-D-galacto-octopyranoside 2-(dihydrogen phosphate). The structural formula for clindamycin phosphate is represented below:

Clindamycin phosphate:

Molecular Formula: C18H34ClN2O8PS Molecular Weight: 504.97

Benzoyl peroxide is an antibacterial and keratolytic agent. The structural formula for benzoyl peroxide is represented below:

Benzoyl peroxide:

Molecular Formula: C14H10O4 Molecular Weight: 242.23

ONEXTON Gel contains the following inactive ingredients: carbomer 980, potassium hydroxide, propylene glycol, and purified water. Each gram of ONEXTON Gel contains 12 mg (1.2%) clindamycin phosphate, equivalent to 10 mg (1%) clindamycin, and 37.5 mg (3.75%) benzoyl peroxide.

12 CLINICAL PHARMACOLOGY

12.1 Mechanism of Action

Clindamycin: Clindamycin is a lincosamide antibacterial [see Microbiology (12.4)].

Benzoyl Peroxide: Benzoyl peroxide is an oxidizing agent with bactericidal and keratolytic effects but the precise mechanism of action is unknown.

12.3 Pharmacokinetics

The systemic absorption of ONEXTON Gel has not been evaluated. The systemic absorption of clindamycin was investigated in an open-label, multiple-dose trial in 16 adult subjects with moderate to severe acne vulgaris treated with 1 gram of a marketed gel containing clindamycin 1%/benzoyl peroxide 2.5% applied to the face once daily for 30 days. This product has the same formulation as ONEXTON Gel but with a lower concentration of benzoyl peroxide. Twelve subjects (75%) had at least one quantifiable clindamycin plasma concentration above the lower limit of quantification (LOQ = 0.5 ng/mL) on Day 1 or Day 30. On Day 1, the mean (± standard deviation) peak plasma concentrations (Cmax) was 0.78 ± 0.22 ng/mL (n=9 with measurable concentrations), and the mean AUC0-t was 5.29 ± 0.81 h.ng/mL (n=4). On Day 30, the mean Cmax was 1.22 ± 0.88 ng/mL (n=10), and the mean AUC0-t was 8.42 ± 6.01 h.ng/mL (n=6). Clindamycin plasma concentrations were below LOQ in all subjects at 24 hours post-dose on the three tested days (Day 1, 15, and 30).

Benzoyl peroxide has been shown to be absorbed by the skin where it is converted to benzoic acid.

12.4 Microbiology

Clindamycin binds to the 50S ribosomal subunits of susceptible bacteria and prevents elongation of peptide chains by interfering with peptidyl transfer, thereby suppressing bacterial protein synthesis.

Clindamycin and benzoyl peroxide individually have been shown to have in vitro activity against Propionibacterium acnes, an organism which has been associated with acne vulgaris. In an in vitro study, the minimum inhibitory concentration (MIC) for benzoyl peroxide against Propionibacterium acnes is 128 mg/L. The clinical significance of this activity against P. acnes is not known.

P. acnes resistance to clindamycin has been documented. Resistance to clindamycin is often associated with resistance to erythromycin.

13 NONCLINICAL TOXICOLOGY

13.1 Carcinogenesis, Mutagenesis, Impairment of Fertility

Carcinogenicity, mutagenicity, and impairment of fertility testing of ONEXTON Gel have not been performed.

Benzoyl peroxide has been shown to be a tumor promoter and progression agent in a number of animal studies. Benzoyl peroxide in acetone at doses of 5 and 10 mg administered topically twice per week for 20 weeks induced skin tumors in transgenic Tg.AC mice. The clinical significance of this is unknown.

Carcinogenicity studies have been conducted with a gel formulation containing 1% clindamycin and 5% benzoyl peroxide. In a 2-year dermal carcinogenicity study in mice, treatment with the gel formulation at doses of 900, 2700, and 15000 mg/kg/day (1.8, 5.4, and 30 times the MRHD for clindamycin and 2.4, 7.2, and 40 times the MRHD for benzoyl peroxide, respectively, based on BSA comparisons) did not cause any increase in tumors. However, topical treatment with a different gel formulation containing 1% clindamycin and 5% benzoyl peroxide at doses of 100, 500, and 2000 mg/kg/day caused a dose-dependent increase in the incidence of keratoacanthoma at the treated skin site of male rats in a 2-year dermal carcinogenicity study in rats. In an oral (gavage) carcinogenicity study in rats, treatment with the gel formulation at doses of 300, 900, and 3000 mg/kg/day (1.2, 3.6, and 12 times the MRHD for clindamycin and 1.6, 4.8, and 16 times the MRHD for benzoyl peroxide, respectively, based on BSA comparisons) for up to 97 weeks did not cause any increase in tumors.

Clindamycin phosphate was not genotoxic in the human lymphocyte chromosome aberration assay. Benzoyl peroxide has been found to cause DNA strand breaks in a variety of mammalian cell types, to be mutagenic in S. typhimurium tests by some but not all investigators, and to cause sister chromatid exchanges in Chinese hamster ovary cells.

Fertility studies have not been performed with ONEXTON Gel or benzoyl peroxide, but fertility and mating ability have been studied with clindamycin. Fertility studies in rats treated orally with up to 300 mg/kg/day of clindamycin (approximately 120 times the MRHD for clindamycin based on BSA comparisons) revealed no effects on fertility or mating ability.

14 CLINICAL STUDIES

The safety and efficacy of once-daily use of ONEXTON Gel was assessed in a 12-week multi-center, randomized, blinded trial in subjects 12 years and older with moderate to severe acne vulgaris. This trial evaluated ONEXTON Gel compared to vehicle gel.

The co-primary efficacy variables for this trial were:

(1) Mean absolute change from baseline at Week 12 in:

- Inflammatory lesion counts
- Non-inflammatory lesion counts

(2) Percent of subjects who had a 2-grade reduction from baseline on an Evaluator’s Global Severity (EGS) score.

The EGS scoring scale used in the clinical trial for ONEXTON Gel is as follows:

Table 2: EGS Scoring Scale

Grade | Description
Clear | Normal, clear skin with no evidence of acne
Almost Clear | Rare non-inflammatory lesions present, with rare non-inflamed papules (papules must be resolving and may be hyperpigmented, though not pink-red)
Mild | Some non-inflammatory lesions are present, with few inflammatory lesions (papules/pustules only; no nodulocystic lesions)
Moderate | Non-inflammatory lesions predominate, with multiple inflammatory lesions evident: several to many comedones and papules/pustules, and there may or may not be one small nodulocystic lesion
Severe | Inflammatory lesions are more apparent, many comedones and papules/pustules, there may or may not be up to 2 nodulocystic lesions
Very Severe | Highly inflammatory lesions predominate, variable number of comedones, many papules/pustules and more than 2 nodulocystic lesions

The results of the trial at Week 12 are presented in Table 3:

Table 3: Results of Phase 3 Trial at Week 12

 | ONEXTON Gel N = 253 | Vehicle Gel N = 245
EGSS:; Clear or Almost Clear | 29% | 15%
2-grade reduction from baseline | 35% | 17%
Inflammatory Lesions:
Mean absolute reduction | 16.3 | 8.2
Mean percent (%) reduction | 60.4% | 31.3%
Non-Inflammatory Lesions:
Mean absolute reduction | 19.2 | 9.6
Mean percent (%) reduction | 51.8% | 27.6%

16 HOW SUPPLIED/STORAGE AND HANDLING

How Supplied

ONEXTON Gel, 1.2%/3.75% is a white to off-white smooth gel supplied as:

NDC 0187-3050-50 50 g pump

Dispensing Instructions for the Pharmacist

- Dispense ONEXTON Gel with a 8-week expiration date.
- Specify “Store at room temperature up to 25°C (77°F). Do not freeze.”

Storage and Handling

- PHARMACIST: Prior to Dispensing: Store in a refrigerator, 2° to 8°C (36° to 46°F).
- PATIENT: After Dispensing: Discard unused portion 8 weeks after date of dispensing. Store at room temperature at or below 25°C (77°F).
- Protect from freezing.
- Store pump upright.
- Keep out of the reach of children
- Keep container tightly closed.

17 PATIENT COUNSELING INFORMATION

Advise the patient to read the FDA-approved patient labeling (Patient Information).

- Patients who develop allergic reactions, such as severe swelling or shortness of breath, should discontinue use and contact their physician immediately.
- ONEXTON Gel may cause irritation, such as erythema, scaling, itching, or burning, especially when used in combination with other topical acne therapies.
- Patients should limit excessive or prolonged exposure to sunlight. To minimize exposure to sunlight, a hat or other clothing should be worn. Sunscreen may also be used.
- ONEXTON Gel may bleach hair or colored fabric.

Distributed by:
Bausch Health US, LLC, Bridgewater, NJ 08807 USA

Manufactured by:
Bausch Health Companies Inc.
Laval, Quebec H7L 4A8, Canada

Patented. See https://patents.ortho-dermatologics.com for US patent information.

ONEXTON is a trademark of Bausch Health Companies Inc. or its affiliates.

© 2025 Bausch Health Companies Inc. or its affiliates

9432706

PATIENT INFORMATION
ONEXTON® (ON-EX-TUN)

(clindamycin phosphate and benzoyl peroxide) gel, 1.2%/3.75%

Important information: ONEXTON Gel is for use on skin only (topical use). Do not use ONEXTON Gel in your mouth, eyes, or vagina.

What is ONEXTON Gel?

ONEXTON Gel is a prescription medicine used on the skin (topical) to treat acne vulgaris in people 12 years of age and older.

It is not known if ONEXTON Gel is safe and effective for use longer than 12 weeks.

It is not known if ONEXTON Gel is safe and effective in children under 12 years of age.

Do not use ONEXTON Gel if you have:

- had an allergic reaction to clindamycin, benzoyl peroxide, lincomycin, or any of the ingredients in ONEXTON Gel. See the end of this leaflet for a complete list of ingredients in ONEXTON Gel.
- Crohn’s disease or ulcerative colitis.
- had inflammation of the colon (colitis) or severe diarrhea with past antibiotic use.

Talk with your doctor if you are not sure if you have any of the conditions listed above.

Before using ONEXTON Gel, tell your doctor about all of your medical conditions, including if you:

- plan to have surgery. ONEXTON Gel may affect how certain medicines work that may be given during surgery.
- are pregnant or plan to become pregnant. It is not known if ONEXTON Gel will harm your unborn baby.
- are breastfeeding or plan to breastfeed. It is not known if ONEXTON Gel passes into your breast milk. Clindamycin when taken by mouth or by injection has been reported to appear in breast milk. Talk to your doctor about the best way to feed your baby during treatment with ONEXTON Gel.
Tell your doctor about all the medicines you take, including prescription and over-the-counter medicines, vitamins and herbal supplements. ONEXTON Gel may affect the way other medicines work and other medicines may affect how ONEXTON Gel works.
- Especially tell your doctor if you take medicine by mouth that contains erythromycin or use products on your skin that contain erythromycin. ONEXTON Gel should not be used with products that contain erythromycin.
- Tell your doctor about any skin products you use. Other skin and topical acne products may increase the irritation of your skin when used with ONEXTON Gel.

Know the medicines you take. Keep a list of them and show it to your doctor and pharmacist when you get a new medicine.

How should I use ONEXTON Gel?

- Use ONEXTON Gel exactly as your doctor tells you to use it. See the detailed “Instructions for Use” for directions about how to apply ONEXTON Gel.
- Your doctor will tell you how long to use ONEXTON Gel.
- Apply ONEXTON Gel to your face 1 time each day.

Before you apply ONEXTON Gel, wash your face gently with a mild soap, rinse with warm water, and pat your skin dry.

What should I avoid while using ONEXTON Gel?

- Limit your time in sunlight. You should avoid using tanning beds or sun lamps during treatment with ONEXTON Gel. If you have to be in sunlight, wear a wide-brimmed hat or other protective clothing, and use sunscreen to cover the treated areas.
- Avoid getting ONEXTON Gel in your hair or on colored fabric. ONEXTON Gel may bleach hair or colored fabric.

What are possible side effects of ONEXTON Gel?

ONEXTON Gel can cause serious side effects including:

- Inflammation of the colon (colitis). Stop using ONEXTON Gel and call your doctor right away if you have severe stomach (abdominal) cramps watery diarrhea, or bloody diarrhea during treatment, and within several weeks after treatment with ONEXTON Gel.
- Allergic reactions. Stop using ONEXTON Gel, call your doctor and get help right away if you have any of the following symptoms during treatment with ONEXTON Gel:
- severe itching
- swelling of your face, eyes, lips, tongue or throat
- trouble breathing

The most common side effects of ONEXTON Gel include burning sensation, skin redness or swelling, itching and rash. Stop using ONEXTON Gel and call your doctor if you have a skin rash or your skin becomes very red, itchy or swollen. Talk to your doctor about any side effect that bothers you or that does not go away.

These are not all of the possible side effects with ONEXTON Gel.

Call your doctor for medical advice about side effects. You may report side effects to FDA at 1-800-FDA-1088.

How should I store ONEXTON Gel?

- Store ONEXTON Gel at room temperature at or below 77°F (25°C).
- Do not freeze ONEXTON Gel.
- Throw away (discard) ONEXTON Gel 8 weeks after date of dispensing.
- Store pump upright.
- Keep the container tightly closed.

Keep ONEXTON Gel and all medicines out of the reach of children.

General information about the safe and effective use of ONEXTON Gel.

Medicines are sometimes prescribed for purposes other than those listed in a Patient Information leaflet. Do not use ONEXTON Gel for a condition for which it was not prescribed. Do not give ONEXTON Gel to other people, even if they have the same condition you have. It may harm them. You can also ask your doctor or pharmacist for information about ONEXTON Gel that is written for healthcare professionals.

What are the ingredients in ONEXTON Gel?

Active Ingredients: clindamycin phosphate and benzoyl peroxide

Inactive Ingredients: carbomer 980, potassium hydroxide, propylene glycol, and purified water.

Distributed by: Bausch Health US, LLC, Bridgewater, NJ 08807 USA

Manufactured by: Bausch Health Companies Inc., Laval, Quebec H7L 4A8, Canada

Patented. See https://patents.ortho-dermatologics.com for US patent information.

ONEXTON is a trademark of Bausch Health Companies Inc. or its affiliates.

© 2025 Bausch Health Companies Inc. or its affiliates

For more information about ONEXTON Gel, call 1-800-321-4576.

This Patient Information has been approved by the U.S. Food and Drug Administration.

Revised: 07/2025

9432706

INSTRUCTIONS FOR USE

ONEXTON® (ON-EX-TUN)
(clindamycin phosphate and benzoyl peroxide) gel, 1.2%/3.75%

Important Information: ONEXTON Gel is for use on skin only (topical use). ONEXTON Gel is not for use in your mouth, eyes or vagina.

Read this Instructions for Use before you start using ONEXTON Gel and each time you get a refill. There may be new information. This information does not take the place of talking with your doctor about your medical condition or treatment.

- Apply ONEXTON Gel to your face 1 time each day as prescribed.
- Before you apply ONEXTON Gel, wash your face gently with a mild soap, rinse with warm water, and pat your skin dry.
- To apply ONEXTON Gel to your face, use the pump to dispense one pea-sized amount of ONEXTON Gel onto your fingertip. See Figure 1.
- One pea-sized amount of ONEXTON Gel should be enough to cover your entire face.

Figure 1

- Dot the one pea-sized amount of ONEXTON Gel onto six areas of your face (chin, left cheek, right cheek, nose, left forehead, right forehead). See Figure 2.

Figure 2

- Spread the gel over your face and gently rub it in. It is important to spread the gel over your entire face. If your doctor tells you to put ONEXTON Gel on other areas of your skin with acne, be sure to ask how much you should use.
- Wash your hands with soap and water after applying ONEXTON Gel.

How should I store ONEXTON Gel?

- Store ONEXTON Gel at room temperature at or below 77°F (25°C).
- Do not freeze ONEXTON Gel.
- Throw away (discard) ONEXTON Gel 8 weeks after date of dispensing.
- Store pump upright.
- Keep the container tightly closed

Keep ONEXTON Gel and all medicines out of the reach of children.

Distributed by: Bausch Health US, LLC, Bridgewater, NJ 08807 USA
Manufactured by: Bausch Health Companies Inc., Laval, Quebec H7L 4A8, Canada

Patented. See https://patents.ortho-dermatologics.com for US patent information.
ONEXTON is a trademark of Bausch Health Companies Inc. or its affiliates.
© 2025 Bausch Health Companies Inc. or its affiliates

This Instructions for Use has been approved by the
U.S. Food and Drug Administration. Revised: July 2025
9432706

PACKAGE LABEL

PRINCIPAL DISPLAY PANEL - 50 gram Carton

NDC 0187-3050-50

Rx only

ONEXTON®
(Clindamycin Phosphate and
Benzoyl Peroxide) Gel, 1.2%/3.75%

For Topical Use Only

Not for ophthalmic, oral or intravaginal use

KEEP OUT OF REACH OF CHILDREN

One premixed 50-gram pump dispenser

Ortho Dermatologics